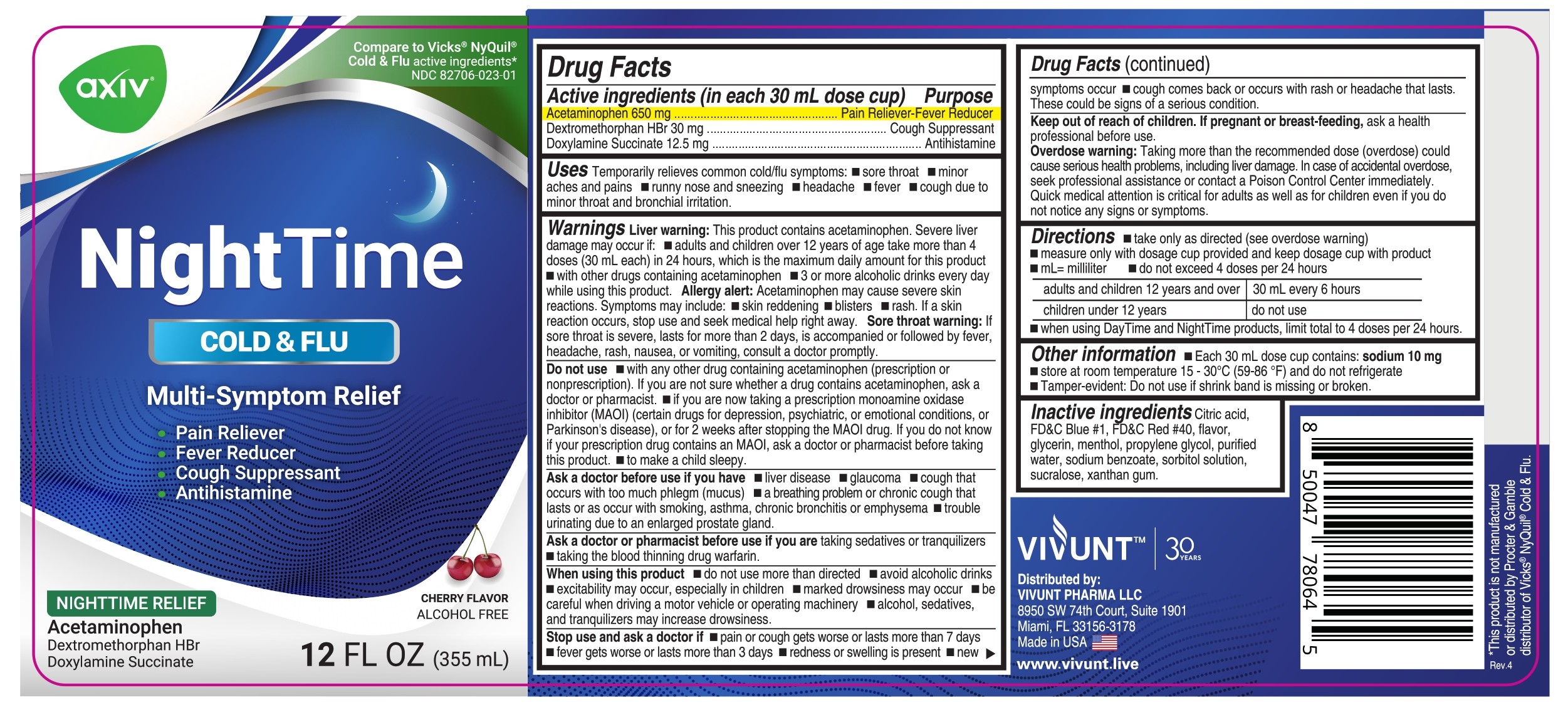 DRUG LABEL: AXIV Night Time - Liquid
NDC: 82706-023 | Form: LIQUID
Manufacturer: VIVUNT PHARMA LLC
Category: otc | Type: HUMAN OTC DRUG LABEL
Date: 20250917

ACTIVE INGREDIENTS: ACETAMINOPHEN 650 mg/30 mL; DEXTROMETHORPHAN HYDROBROMIDE 30 mg/30 mL; DOXYLAMINE SUCCINATE 12.5 mg/30 mL
INACTIVE INGREDIENTS: CITRIC ACID MONOHYDRATE; FD&C BLUE NO. 1; FD&C RED NO. 40; GLYCERIN; MENTHOL, UNSPECIFIED FORM; PROPYLENE GLYCOL; WATER; SODIUM BENZOATE; SORBITOL SOLUTION; SUCRALOSE; XANTHAN GUM

AXIV Night Time Cold & Flu - Liquid

Drug Facts

ACTIVE INGREDIENT

PURPOSE

Active ingredients (in each 30 mL dose cup) | Purpose
Acetaminophen 650 mg | Pain reliever/fever reducer
Dextromethorphan HBr 30 mg | Cough suppressant
Doxylamine succinate 12.5 mg | Antihistamine

Uses

Temporarily relieves common cold/flu symptoms:

- sore throat
- minor aches & pains
- runny nose & sneezing
- headache
- fever
- cough due to minor throat & bronchial irritation

Warnings

Liver warning

This product contains acetaminophen. Severe liver damage may occur if:

- adults and children over 12 years of age take more than 4 doses (30 mL each) in 24 hrs, which is the maximum daily amount for this product
- with other drugs containing acetaminophen
- 3 or more alcoholic drinks daily while using this product

Allergy alert

Acetaminophen may cause severe skin reactions. Symptoms may include:

- skin reddening
- blisters
- rash

If a skin reaction occurs, stop use and seek medical help right away.

Sore throat warning

If sore throat is severe, lasts for more than 2 days, is accompanied or followed by fever, headache, rash, nausea, or vomiting, consult a doctor promptly.

Do not use

- with any other drug containing acetaminophen (prescription or nonprescription). If you are not sure whether a drug contains acetaminophen, ask a doctor or pharmacist.
- if you are now taking a prescription monoamine oxidase inhibitor (MAOI) (certain drugs for depression, psychiatric, or emotional conditions, or Parkinson's disease), or for 2 weeks after stopping the MAOI drug. If you do not know if your prescription drug contains an MAOI, ask a doctor or pharmacist before taking this product.
- if you have ever had an allergic reaction to this product or any of its ingredients
- to make a child sleep

Ask a doctor before use if you have

- liver disease
- glaucoma
- cough that occurs with too much phlegm (mucus)
- a breathing problem or chronic cough that lasts or as occurs with smoking, asthma, chronic bronchitis, or emphysema
- trouble urinating due to enlarged prostate gland

Ask a doctor or pharmacist before use if you are

- taking sedatives or tranquilizers
- taking the blood thinning drug warfarin

When using this product

- do not use more than directed
- excitability may occur, especially in children
- marked drowsiness may occur
- avoid alcoholic drinks
- be careful when driving a motor vehicle or operating machinery
- alcohol, sedatives, and tranquilizers may increase drowsiness

Stop use and ask a doctor if

- pain or cough gets worse or lasts more than 7 days
- fever gets worse or lasts more than 3 days
- redness or swelling is present
- new symptoms occur
- cough comes back or occurs with rash or headache that lasts.

These could be signs of a serious condition.

Keep out of reach of children.

If pregnant or breast-feeding

ask a health professional before use.

Overdose warning

Taking more than the recommended dose (overdose) could cause serious health problems, including liver damage. In case of overdose, get medical help or contact a Poison Control Center right away. Quick medical attention is critical for adults as well as for children even if you do not notice any signs or symptoms

Directions

- take only as directed (see overdose warning)
- measure only with dosage cup provided and keep dosage cup with product
- mL = milliliter
- do not exceed 4 doses per 24 hours
- when using DayTime and NightTime products, limit total to 4 doses per 24 hours

adults and children 12 years and over | 30 mL every 6 hours
children under 12 years | do not use

Other information

- Each 30 mL dose cup contains: sodium 10 mg
- Store at room temperature 15 - 30°C (59 - 89°F) and do not refrigerate
- Tamper evident: Do not use if shrink band is missing or broken

Inactive ingredients

Citric acid, FD&C Blue #1, FD&C Red #40, flavor, glycerin, menthol, propylene glycol, purified water, sodium benzoate, sorbitol solution, sucralose, xanthan gum

Distributed by:

VIVUNT PHARMA LLC
8950 SW 74th. Court. Suite 1901

Miami, FL 33156-3178

Made in USA

www.vivunt.live

PRINCIPAL DISPLAY PANEL

Compare to VICKS®NyQuil®

Cold & Flu active ingredients*

NDC 82706-023-01

AXIV - NightTime

COLD&FLU

Multi-Symptom Relief

- Pain Reliever
- Fever Reducer
- Cough Suppresant
- Antihistamine

Nighttime Relief

Acetaminophen, Dextromethorphan HBr, Doxylamine Succinate

12 FL OZ (355 mL)

*This product is not manufactured or distributed by The Procter &Gamble Company, owner of registered trademarks Vicks® NyQuil®